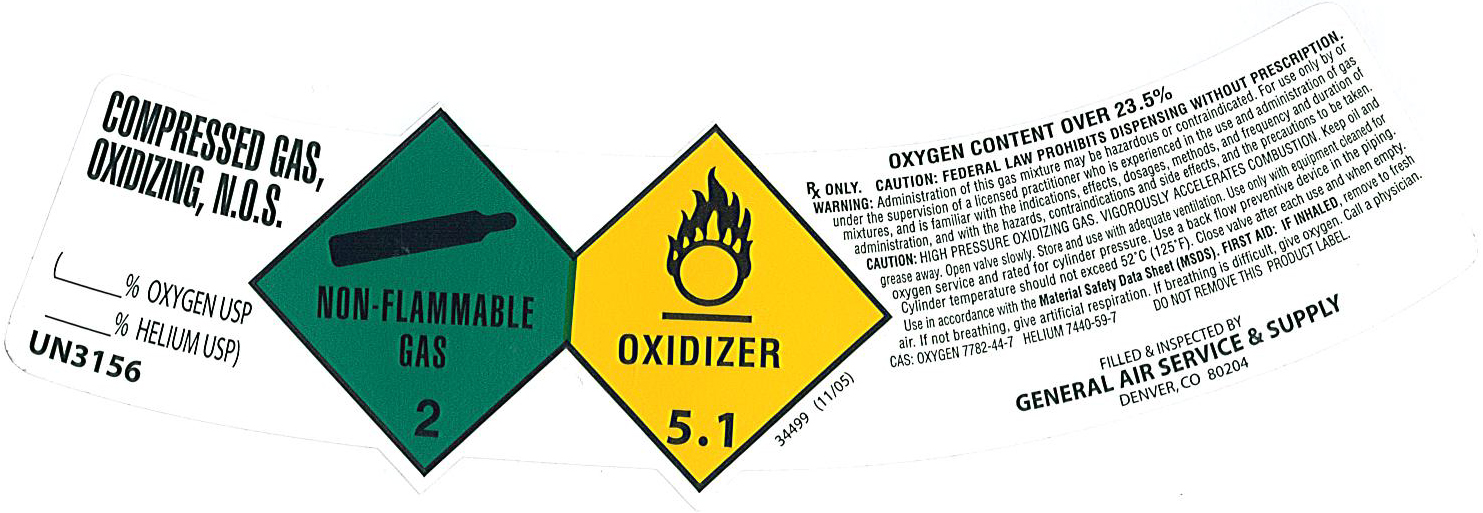 DRUG LABEL: Helium/Oxygen Mixture 70/30
NDC: 21220-128 | Form: GAS
Manufacturer: General Air Service & Supply Co
Category: prescription | Type: HUMAN PRESCRIPTION DRUG LABEL
Date: 20101222

ACTIVE INGREDIENTS: Helium 700 mL/1 L; Oxygen 300 mL/1 L

Helium/Oxygen Mixture 70/30

PACKAGE LABEL

COMPRESSED GAS, OXIDIZING, N.O.S. (% OXYGEN USP %HELIUM USP) UN3156
NON-FLAMMABLE GAS 2 OXIDIZER 5.1 34499 (11/05)
OXYGEN CONTENT OVER 23.5 %
Rx only. CAUTION: FEDERAL LAW PROHIBITS DISPENSING WITHOUT A PRESCRIPTION. WARNING: Administration of this gas mixture may be hazardous or contraindicated. For use only by or under the supervision of a licensed practitioner who is experienced in the use and administration of gas mixtures, and is familiar with the indications, effects, dosages, methods, and frequency and duration of administration, and with the hazards, contraindications and side effects, and the precautions to be taken. CAUTION: HIGH PRESSURE OXDIZING GAS. VIGOROUSLY ACCELERATES COMBUSTION. Keep oil and grease away. Open valve slowly. Store and use with adequate ventilation. Use only with equipment cleaned for oxygen service and rated for cylinder pressure. Use a back flow preventive device in the piping. Cylinder temperature should not exceed 52C (125F). Close valve after each use and when empty. Use in accordance with the Material Safety Data Sheet (MSDS). FIRST AID: IF INHALED, remove to fresh air. If not breathing, give artificial respiration. If breathing is difficult, give oxygen. Call a physician. CAS: OXYGEN 7782-44-7 HELIUM 7440-59-7 DO NOT REMOVE THIS PRODUCT LABEL.
FILLED and INPSECTED BY GENERAL AIR SERVICE and SUPPLY DENVER, CO 80204